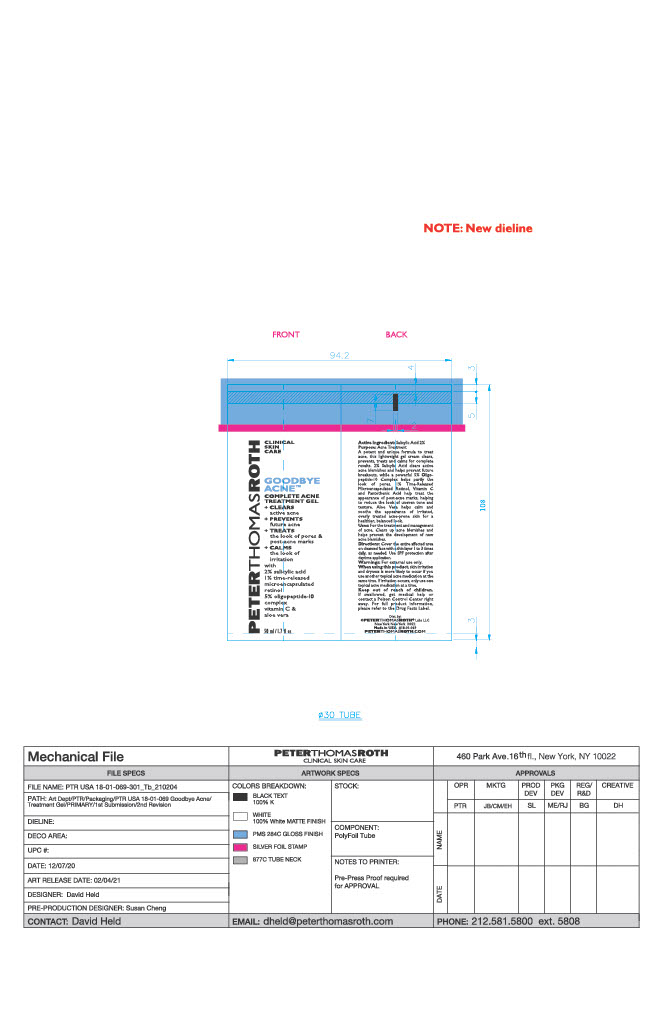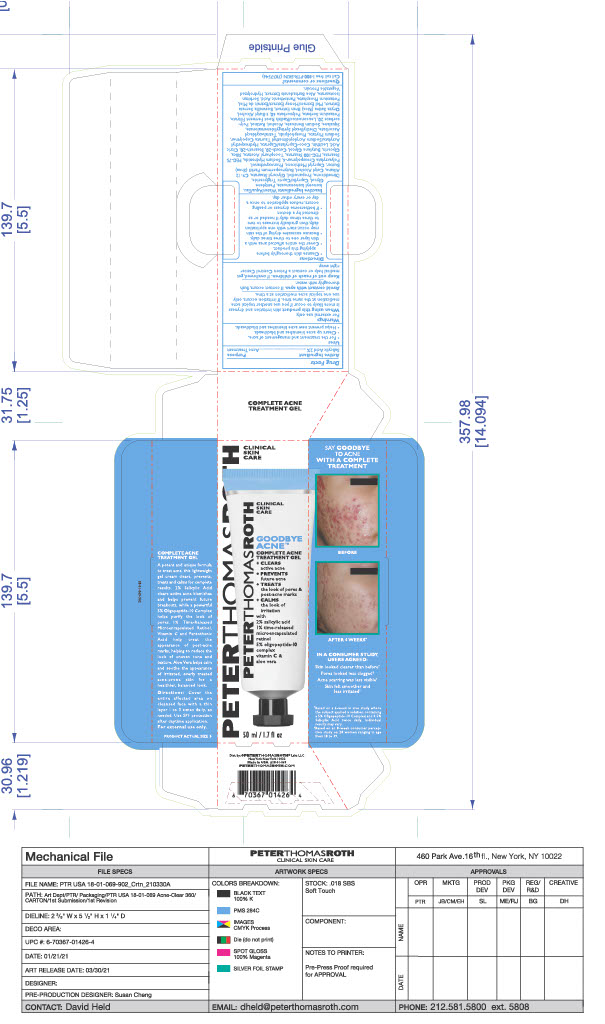 DRUG LABEL: GOODBYE ACNE Complete treatment gel
NDC: 54031-069 | Form: GEL
Manufacturer: Peter Thomas Roth, LLC
Category: otc | Type: HUMAN OTC DRUG LABEL
Date: 20231114

ACTIVE INGREDIENTS: SALICYLIC ACID 0.9638 g/48.19 g
INACTIVE INGREDIENTS: PEG-75 STEARATE; COCO-CAPRYLATE/CAPRATE; ISONONYL ISONONANOATE; TETRAHEXYLDECYL ASCORBATE; ALCOHOL; HONEY; POTASSIUM SORBATE; DIMETHICONE; .ALPHA.-TOCOPHEROL ACETATE; GLYCERYL MONOSTEARATE; CETYL ALCOHOL; LEUCONOSTOC/RADISH ROOT FERMENT FILTRATE; POTASSIUM PHOSPHATE, UNSPECIFIED FORM; WATER; SORBITAN ISOSTEARATE; HYDROLYZED SOY PROTEIN (ENZYMATIC; 2000 MW); C9-12 ALKANE; SILICON DIOXIDE; BUTYLENE GLYCOL; POLYSORBATE 20; SHEA BUTTER; PENTYLENE GLYCOL; MEDIUM-CHAIN TRIGLYCERIDES; PROPANEDIOL; SODIUM HYDROXIDE; PHYTATE SODIUM; TERT-BUTYL ALCOHOL; INDIAN FRANKINCENSE; RICE BRAN; CAPRYLYL TRISILOXANE; CITRIC ACID MONOHYDRATE; GLYCERIN; DIETHYLHEXYL SYRINGYLIDENEMALONATE; RETINOL; POLYSORBATE 60; CETETH-20; PEG-100 STEARATE; PHENOXYETHANOL; AMMONIUM ACRYLOYLDIMETHYLTAURATE, DIMETHYLACRYLAMIDE, LAURYL METHACRYLATE AND LAURETH-4 METHACRYLATE COPOLYMER, TRIMETHYLOLPROPANE TRIACRYLATE CROSSLINKED (45000 MPA.S); STEARETH-20; SQUALANE; SODIUM BENZOATE; ALOE; LECITHIN, SOYBEAN; PANTOTHENIC ACID; HYDROXYETHYL ACRYLATE/SODIUM ACRYLOYLDIMETHYL TAURATE COPOLYMER (45000 MPA.S AT 1%)

GOODBYE ACNE Complete treatment gel

Active Ingredient

Salicylic Acid 2%

Active Ingredient Purpose

Salicylic Acid 2%.................................................................Acne treatment

Uses

- For the treatment and management of acne.
- Clears up acne blemishes and blackheads.
- Helps prevent new acne blemishes and blackheads.

Warnings

For external use only.

When using this product skin irritation and dryness is more likely to occur if you use another topical acne medication at the same time. If irritation occurs, only use one topical acne medication at a time.

Avoid contact with eyes. If contact occurs, flush thoroughly with water.

Keep out of reach of children. If swallowed, get medical help or contact a Poison Control center right away.

Directions

- Cleanse skin thoroughly before applying this product.
- Cover the entire affected area with a thin layer one to three times daily.
- Because excessive drying of the skin may occur, start with one application daily, the gradually increase to two to three times daily if needed or as direrected by a doctor.
- If bothersome dryness or peeling occurs, reduce application to once a day or every other day.

Inactive Ingredients

Water/Aqua/Eau, Isononyl Isononanoate, Pentylene Glycol, Caprylic/Capric Triglyceride, Dimethicone, Propanediol, Glyceryl Stearate, C9-12 Alkane, Cetyl Alcohol, Butyrospermum Parkii (Shea) Butter, Caprylyl Methicone, Phenoxyethanol,Polyacrylate Crosspolymer-6, Sodium Hydroxide, PEG-75 Stearate, PEG-100 Stearate, Tocopheryl Acetate, Silica, Glycerin, Butylene Glycol, Ceteth-20, Steareth-20, Citric Acid, Lecithin, Coco-Caprylate/Caprate, Hydroxyethyl Acrylate/Sodium Acryloyldimethyl Taurate Copolymer, Sodium Phytate, Phospholipids, Tetrahexyldecyl Ascorbate, Diethylhexyl Syringylidenemalonate, Squalane,Sodium Benzoate, Alcohol, Retinol, Polysorbate 20, Leuconostoc/Radish Root Ferment Filtrate, Potassium Sorbate, Polysorbate 60, t-Butyl Alcohol, Oryza Sativa (Rice) Bran Extract, Boswellia Serrata Extract, Honey Extract, Potassium Phosphate, Pantothenic Acid, Sorbitan Isostearate, Aloe Barbadensis Extract, Hydrolyzed Vegetable Protein

Questions or comments?

Call toll free 1-800-PTR-SKIN (787-7546)